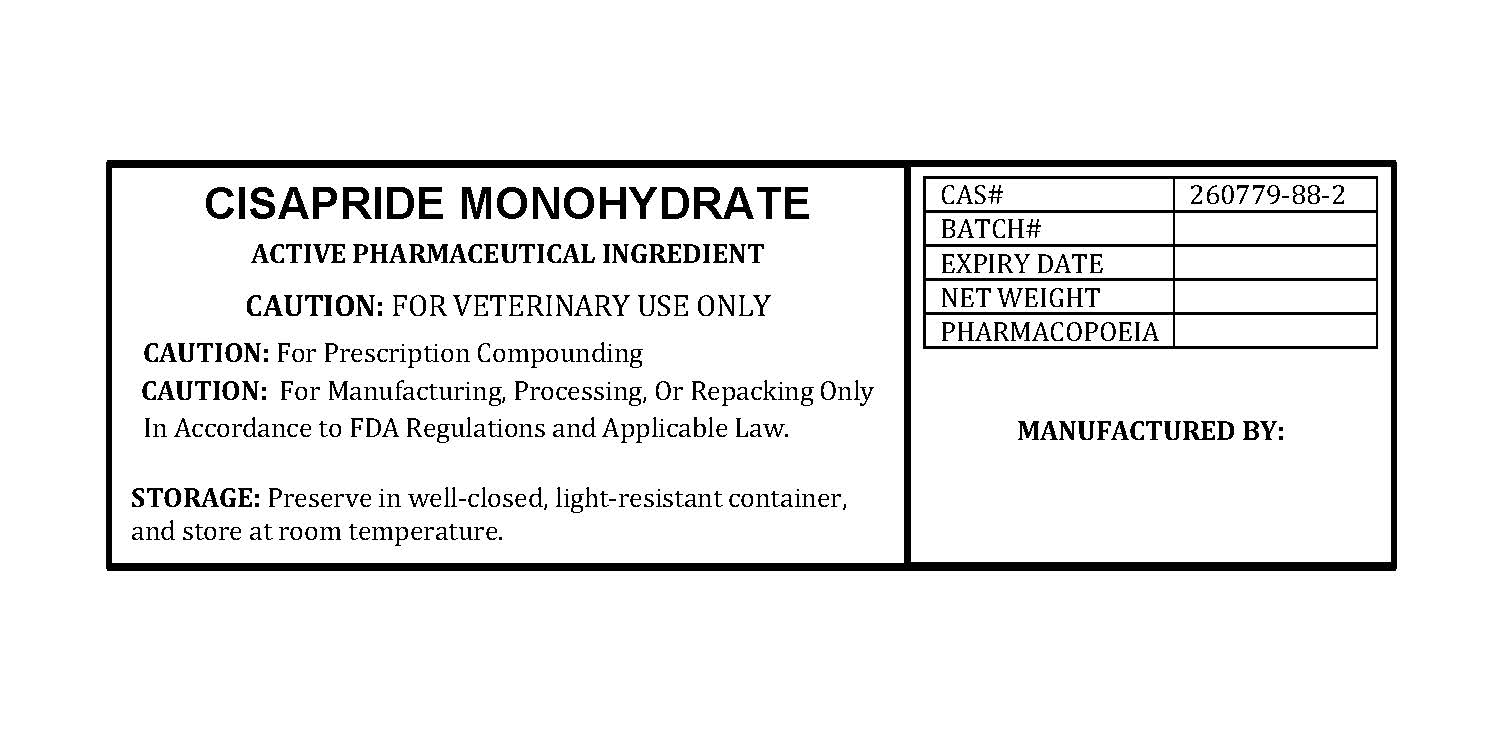 DRUG LABEL: CISAPRIDE MONOHYDRATE
NDC: 86184-047 | Form: POWDER
Manufacturer: MAEDA INC
Category: other | Type: BULK INGREDIENT - ANIMAL DRUG
Date: 20251020

ACTIVE INGREDIENTS: CISAPRIDE MONOHYDRATE 1 g/1 g

CISAPRIDE MONOHYDRATE

PACKAGE LABEL

cisapridemonohydratelabel.jpg